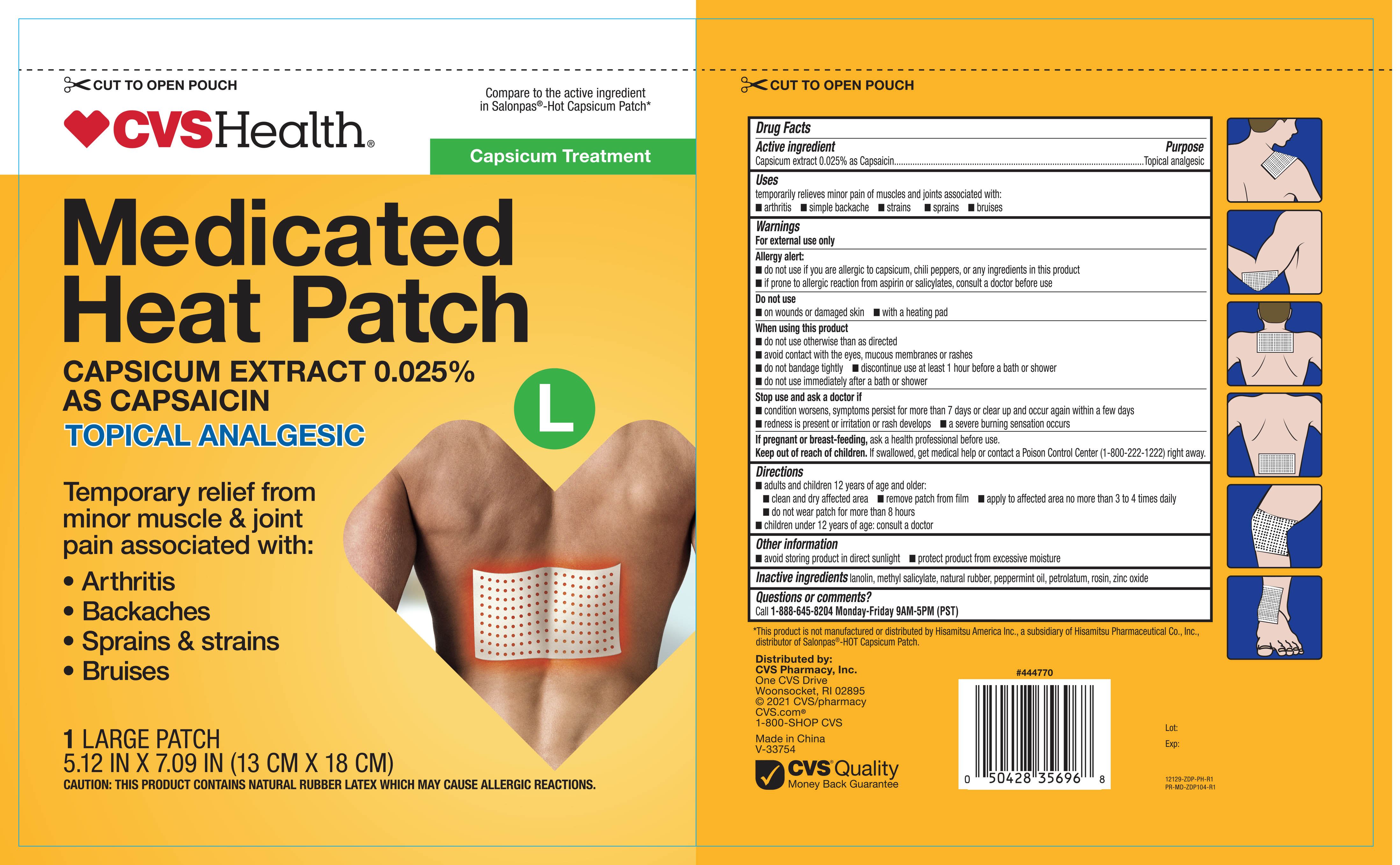 DRUG LABEL: CVS Medicated Heat 1 ct
NDC: 59779-770 | Form: PATCH
Manufacturer: CVS Pharmacy, Inc.
Category: otc | Type: HUMAN OTC DRUG LABEL
Date: 20251031

ACTIVE INGREDIENTS: CAPSAICIN 0.025 g/1 g
INACTIVE INGREDIENTS: ROSIN; NATURAL LATEX RUBBER; LANOLIN; METHYL SALICYLATE; PEPPERMINT OIL; PETROLATUM; ZINC OXIDE

CVS Medicated Heat Capsicum Patch 1ct (NBE Salonpas) 12129 2021 ZDP

Active ingredient Purpose

Capsicum Extract 0.025% as Capsaicin ................. Topical Analgesic

Uses

For temporary relief of minor aches and pains of muscles & joints associated with:

- Simple backache
- Arthritis
- Strains
- Bruises
- Sprains

Warnings

For external use only

Allergy alert:

- do not use if you are allergic to capsicum, chili peppers, or any ingredients in this product
- if prone to allergic reaction from aspirin or salicylates, consult a doctor before use

Do not use

- on wounds or damaged skin
- with a heating pad

When using this product:

- do not use otherwise than as directed
- avoid contact with the eyes, mucous membranes or rashes
- do not bandage tightly
- discontinue use at least 1 hour before a beath or shower
- do not use immediately after a bath or shower

Stop use and ask a doctor if:

- conditions worsens, symptoms persist for more than 7 days or clear up and occur again within a few days
- redness is present or irritation or rash develops
- a severe burning sensation occurs

PREGNANCY OR BREAST FEEDING

If pregnant or breast-feeding, ask a health professional before use.

Keep out of reach of children

If swallowed, get medical help or contact a Poision Control Center right away

Directions

Adults and Children 12 years of age and over:

- Clean and dry affected area
- Remove patch from film
- Apply to affected area not more than 3 to 4 times daily
- do not wear patch for more than 8 hours
- children under 12 years of age: consult a doctor

Other information

- Avoid storing product in direct sunlight
- Protect product from excessive moisture

Inactive ingredietns

lanolin, methyl salicylate, natural rubber, peppermint oil, petrolatum, rosin, zinc oxide

DOSAGE AND ADMINISTRATION

DISTRIBUTED BY:

CVS Pharmacy, Inc.

Woonsocket, RI 02895

Made in China